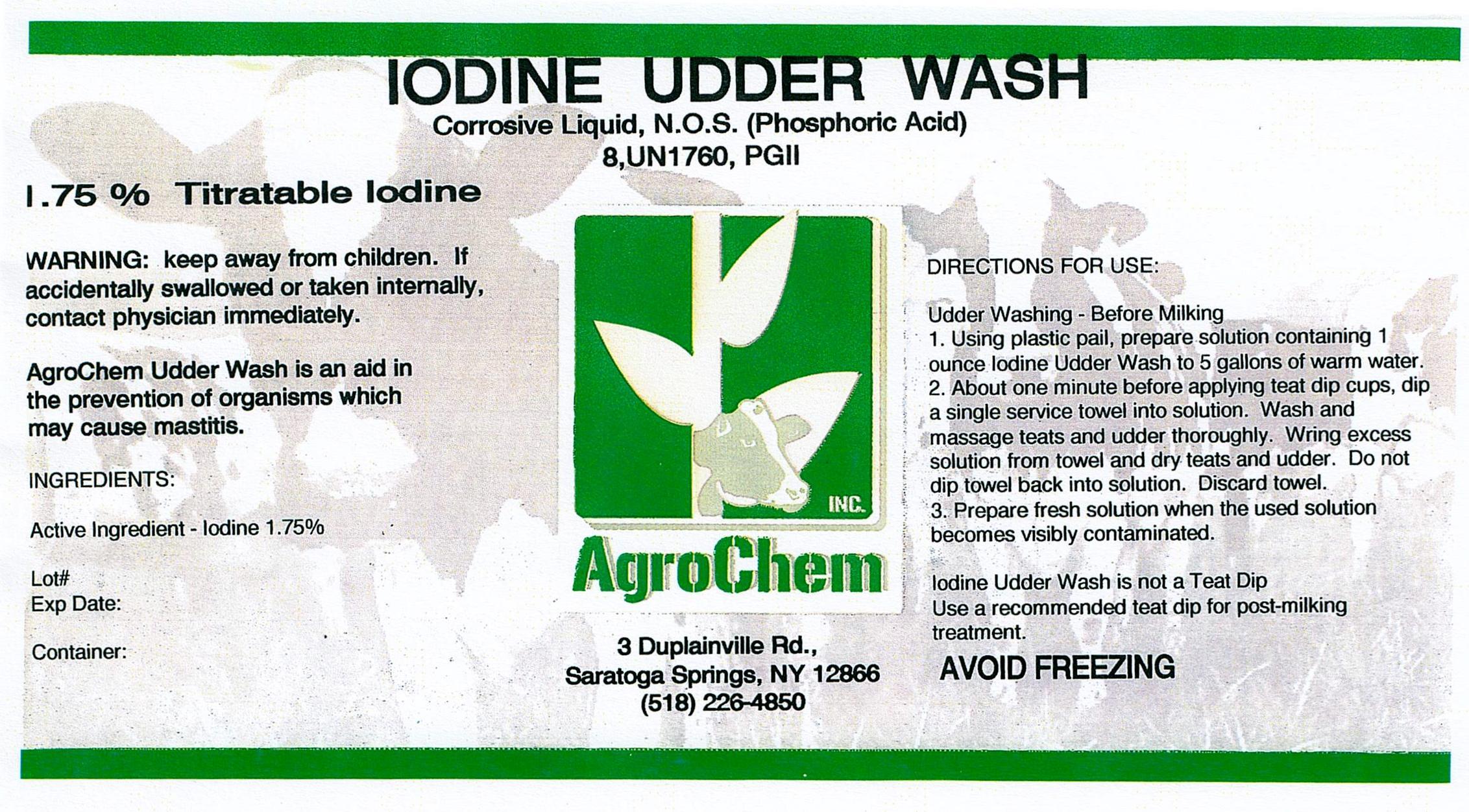 DRUG LABEL: Udder Wash 1.75% Iodine
NDC: 17307-4704 | Form: SOLUTION
Manufacturer: AgroChem Inc
Category: animal | Type: OTC ANIMAL DRUG LABEL
Date: 20130910

ACTIVE INGREDIENTS: IODINE 0.0175 kg/1 kg
INACTIVE INGREDIENTS: WATER 0.66 kg/1 kg; PHOSPHORIC ACID 0.10 kg/1 kg; C10-16 PARETH-1 0.03 kg/1 kg; C9-11 PARETH-3 0.03 kg/1 kg

Udder Wash 1.75% Iodine

DESCRIPTION

Corrosive Liquid, N.O.S (Phosphoric Acid)

8, UN1760, PGll

ACTIVE INGREDIENT

1.75 % Titratable Iodine

WARNINGS

WARNING: keep away from children. If

accidentally swallowed or taken internally,

contact physician immediately.

DESCRIPTION

AgroChem Udder Wash is an aid in

the prevention of orangisms which

may cause mastitis.

ACTIVE INGREDIENT

INGREDIENTS:

Active Ingredient - Iodine 1.75%

DIRECTIONS FOR USE:

Udder Washing - Before Milking

1. Using plastic pail, prepare solution containing 1

ounce Iodine Udder Wash to 5 gallons of warm water.

2. About one minute before applying teat dip cups, dip

a single service towel into solution. Wash and

massage teats and udder thoroughly. Wring excess

solution from towel and dry teats and udder. Do not

dip towel back into solution. Discard towel.

3. Prepare fresh solution when the used solution

becomes visibly contaminated.

Iodine Udder Wash is not a Teat Dip

Use recommended teat dip for post-milking

treatment.

AVOID FREEZING